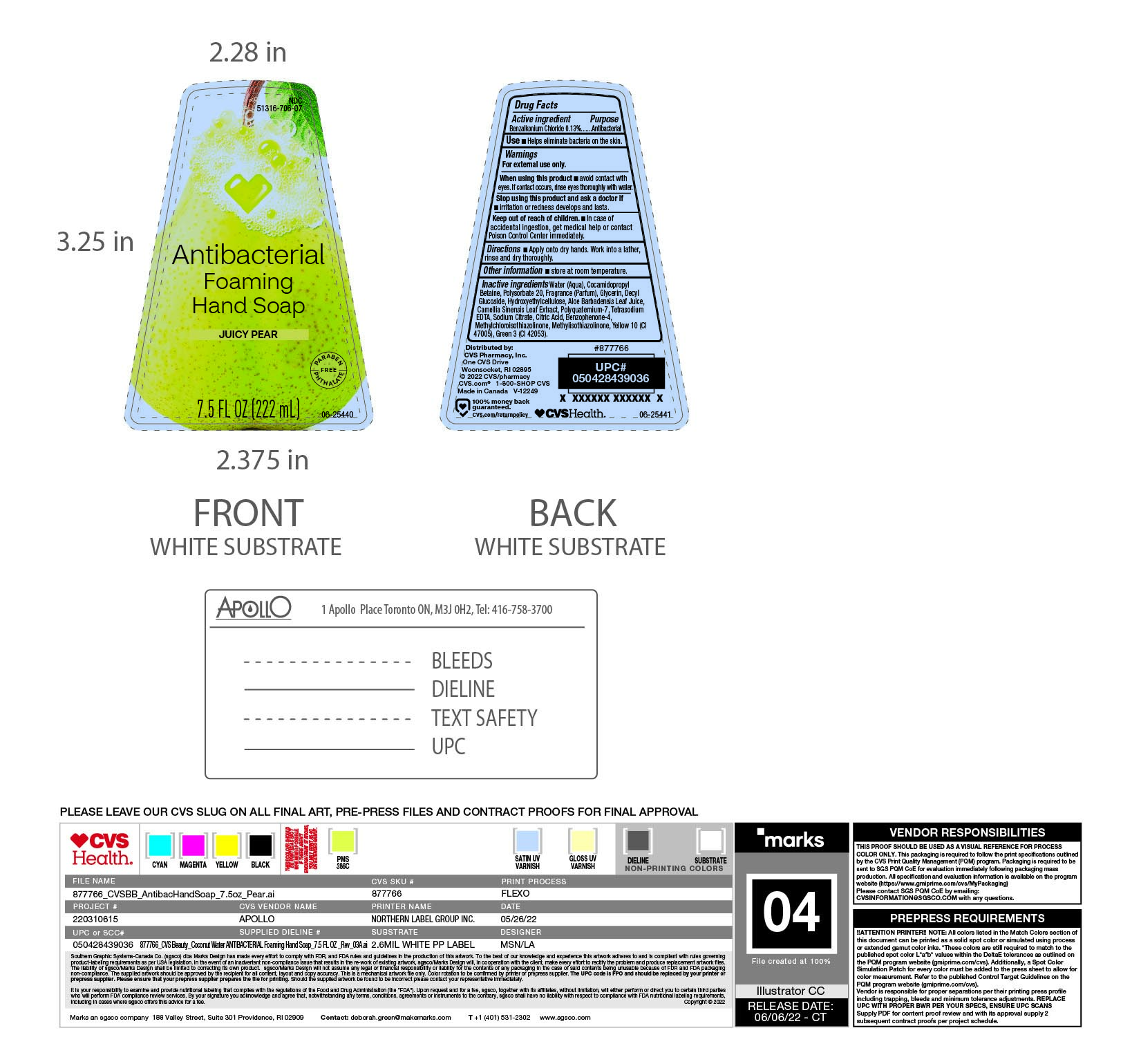 DRUG LABEL: Handsoap
NDC: 51316-706 | Form: SOAP
Manufacturer: CVS PHARMACY, INC
Category: otc | Type: HUMAN OTC DRUG LABEL
Date: 20250207

ACTIVE INGREDIENTS: BENZALKONIUM CHLORIDE 130 mg/100 mL
INACTIVE INGREDIENTS: ALOE VERA LEAF; CITRIC ACID MONOHYDRATE; D&C YELLOW NO. 10; FD&C GREEN NO. 3; POLYQUATERNIUM-7 (70/30 ACRYLAMIDE/DADMAC; 1600 KD); SODIUM CITRATE; COCAMIDOPROPYL BETAINE; POLYSORBATE 20; FRAGRANCE CLEAN ORC0600327; GLYCERIN; DECYL GLUCOSIDE; HYDROXYETHYL CELLULOSE (2000 CPS AT 1%); GREEN TEA LEAF; SULISOBENZONE; EDETATE SODIUM; METHYLCHLOROISOTHIAZOLINONE; METHYLISOTHIAZOLINONE; WATER

NDC- 51316-706

ACTIVE INGREDIENT

Benzalkonium Chloride

PURPOSE

Hand washing

WARNINGS

KEEP OUT OF REACH OF CHILDREN

Incase of accidental ingestion, get medical help or contact poison control centre immediately.

DOSAGE AND ADMINISTRATION

Apply onto dry hands, work into a lather, rinse and dry throughly.

INACTIVE INGREDIENT

Water(Aqua), Cocamidopropyl Betaine, Polysorbate 20, Fragrance (Parfum), Glycerin, Decyl Glucoside, Hydroxyethylcellulose, Aloe Barbadensis, Camellia Sinensis Leaf Extract,Polyquaternium-7, Tetrasodium EDTA, Sodium Citrate, Citric Acid, Benzophenone -4, Methylcholoroisothiazolinone, Methylisothiazolinone, Yellow 10 (Cl 47005), Green 3 (Cl 42053)

INDICATIONS AND USAGE

Helps eliminate bacteria on the skin